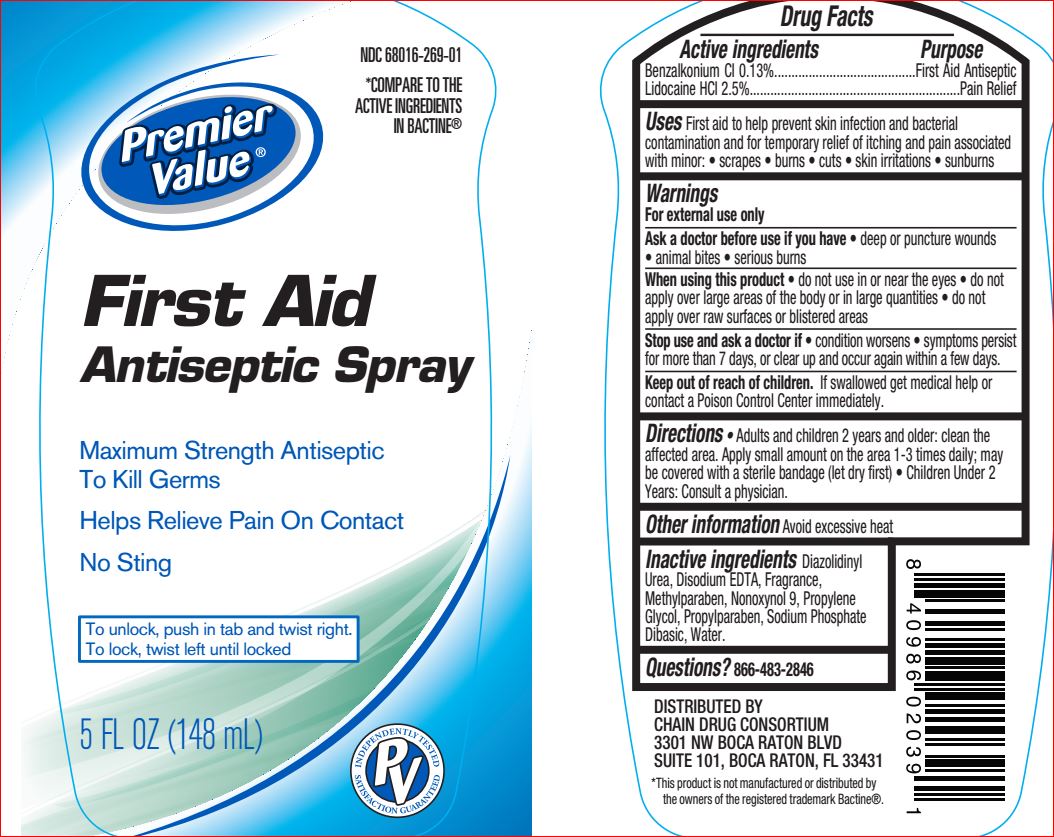 DRUG LABEL: First Aid Antiseptic
NDC: 68016-269 | Form: SPRAY
Manufacturer: Premier Value
Category: otc | Type: HUMAN OTC DRUG LABEL
Date: 20180710

ACTIVE INGREDIENTS: LIDOCAINE HYDROCHLORIDE 25 mg/1 mL; BENZALKONIUM CHLORIDE 1.3 mg/1 mL
INACTIVE INGREDIENTS: Diazolidinyl Urea; EDETATE DISODIUM ANHYDROUS; Methylparaben; NONOXYNOL-9; Propylene Glycol; Propylparaben; SODIUM PHOSPHATE, DIBASIC, ANHYDROUS; Water

Drug Facts

Active ingredients Purpose

Benzalkonium 0.13% First Aid Antiseptic

Lidocaine HCl 2.5% Pain Relieving Spray

Uses

First aid to help prevent bacterial contamination or skin infection, and for temporary relief of pain and itching associated with minor: cuts, scrapes, burns, sunburn, skin irritations

Warnings

For external use only

Ask a doctor before use if you have

- deep or puncture wounds
- animal bites
- serious burns

When using this product

- do not use in or near the eyes
- do not apply over large area of the body or in large quantities
- do not apply over raw surfaces or blistered areas

Stop use and ask a doctor if

- condition worsens
- symptoms persist for more than 7 days, or clear up and occur again within a few days

Keep out of reach of children

If swallowed get medical help or contact a Poison Control Center right away

Directions

• Adults and children 2 years and older: clean the affected area. Apply small amount on the area 1-3 times daily; may be covered with a sterile bandage (let dry first) • Children Under 2 years: Consult a physician.

Other information

Avoid excessive heat

Inactive ingredients

Diazolidinyl Urea, Disodium EDTA, Fragrance, Methylparaben, Nonoxynol 9, Propylene Glycol, Propylparaben, Sodium Phosphate Dibasic, Water